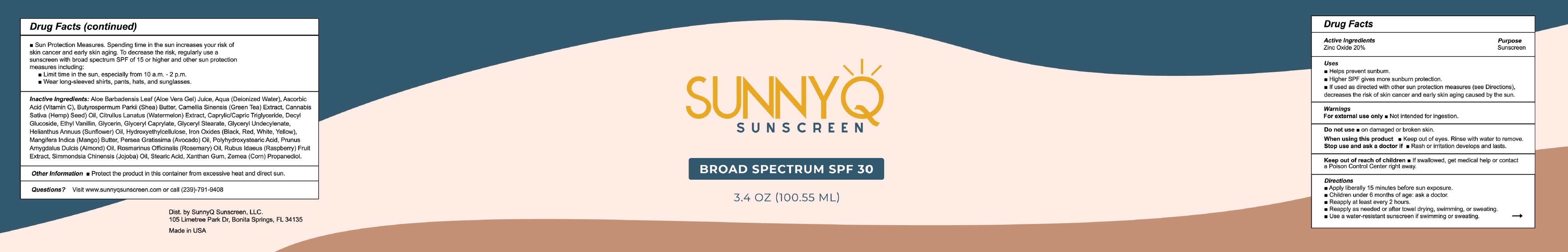 DRUG LABEL: SUNNY Q Broad Spectrum SPF-30
NDC: 81738-138 | Form: LOTION
Manufacturer: Sunny Q Sunscreen LLC
Category: otc | Type: HUMAN OTC DRUG LABEL
Date: 20231111

ACTIVE INGREDIENTS: ZINC OXIDE 200 mg/1 mL
INACTIVE INGREDIENTS: ALOE VERA LEAF; WATER; ASCORBIC ACID; SHEA BUTTER; GREEN TEA LEAF; CANNABIS SATIVA SEED; WATERMELON; MEDIUM-CHAIN TRIGLYCERIDES; DECYL GLUCOSIDE; ETHYL VANILLIN; GLYCERIN; GLYCERYL CAPRYLATE; GLYCERYL MONOSTEARATE; GLYCERYL 1-UNDECYLENATE; HELIANTHUS ANNUUS FLOWERING TOP; HYDROXYETHYL CELLULOSE, UNSPECIFIED; FERRIC OXIDE RED; MANGO; AVOCADO OIL; ALMOND; ROSEMARY; RASPBERRY; JOJOBA OIL; STEARIC ACID; XANTHAN GUM; CORN

SUNNY Q Broad Spectrum SPF-30

Active Ingredients

Zinc Oxide 20%

Purpose

Sunscreen

Uses

- Helps prevent sunburn.
- Higher SPF gives more sunburn protection.
- If used as directed with other sun protection measures (see Directions), decreases the risk of skin cancer and early skin aging caused by the sun.

Warnings

For external use only

- Not intended for ingestion.

Do not use

- on damaged or broken skin.

When using this product:

- Keep out of eyes. Rinse with water to remove.

Stop use and ask a doctor if

- Rash or irritation develops and lasts.

Keep out of reach of children.

- If swallowed, get medical help or contact a Poison Control Center right away.

Directions

• Apply liberally 15 minutes before sun exposure. • Children under 6 months of age: ask a doctor. • Reapply at least every 2 hours. • Reapply as needed or after towel drying, swimming, or sweating. • Use a water-resistant sunscreen if swimming or sweating. • Sun Protection Measures. Spending time in the sun increases your risk of skin cancer and early skin aging. To decrease the risk, regularly use a sunscreen with broad spectrum SPF of 15 or higher and other sun protection measures including: • Limit time in the sun, especially from 10 a.m. - 2 p.m. • Wear long-sleeved shirts, pants, hats, and sunglasses.

Inactive Ingredients:

Aloe Barbadensis Leaf (Aloe Vera Gel) Juice, Aqua (Deionized Water), Ascorbic Acid (Vitamin C), Butyrospermum Parkii (Shea) Butter, Camellia Sinensis (Green Tea) Extract, Cannabis Sativa (Hemp Seed) Oil, Citrullus Lanatus (Watermelon) Extract, Caprylic/Capric Triglyceride, Decyl Glucoside, Ethyl Vanillin, Glycerin, Glyceryl Caprylate, Glyceryl Stearate, Glyceryl Undecylenate, Helianthus Annuus (Sunflower) Oil, Hydroxyethylcellulose, Iron Oxides (Black, Red, White, Yellow), Mangifera Indica (Mango) Butter, Persea Gratissima (Avacado) Oil, Polyhydroxystearic Acid, Prunus Amygdalus Dulcis (Almond) Oil, Rosmarinus Officinalis (Rosemary) Oil, Rubus Idaeus (Raspberry) Fruit Extract, Simmondsia Chinensis (Jojoba) Oil, Stearic Acid, Xanthan Gum, Zemea (Corn) Propanediol.

Other Information

- Protect the product in this container from excessive heat and direct sun.

Questions?

Visit www.sunnyqsunscreen.com or call (239)-791-9408